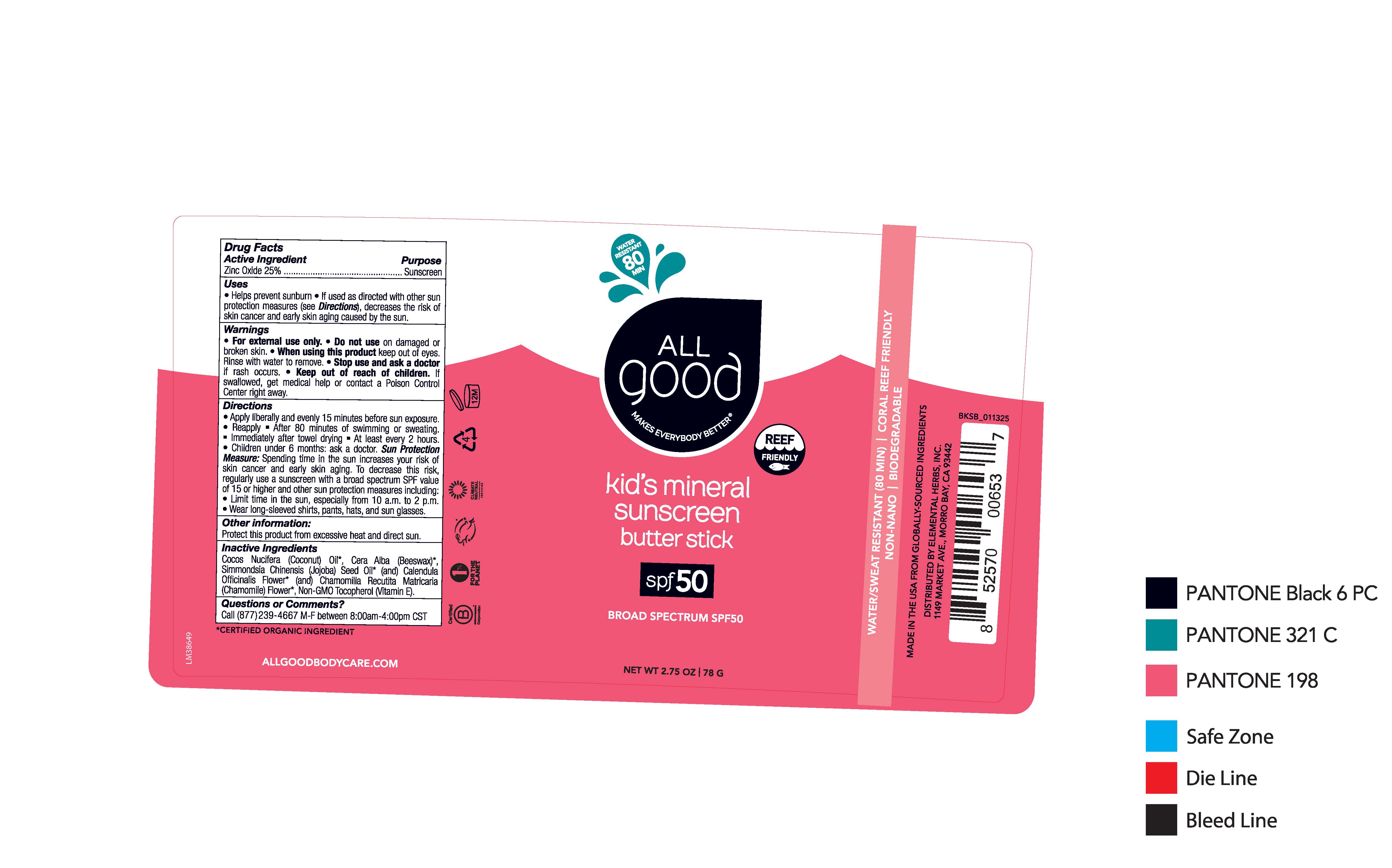 DRUG LABEL: All Good kids mineral sunscreen butter stick SPF 50
NDC: 75786-230 | Form: OINTMENT
Manufacturer: Elemental Herbs, Inc.
Category: otc | Type: HUMAN OTC DRUG LABEL
Date: 20250505

ACTIVE INGREDIENTS: ZINC OXIDE 25 g/100 g
INACTIVE INGREDIENTS: MATRICARIA CHAMOMILLA LEAF; COCONUT OIL; TOCOPHEROL; CALENDULA OFFICINALIS FLOWER; WHITE WAX; JOJOBA OIL

All Good kid's mineral sunscreen butter stick SPF 50 (English-Only / US Label)

Drug Facts

Active Ingredient

Zinc Oxide 25%

Purpose

Sunscreen

Uses

- Helps prevent sunburn
- If used as directed with other sun protection measures (see Directions), decreases the risk of skin cancer and early skin aging caused by the sun.

Warnings

- For external use only

Do not use on damaged or broken skin.

When using this product keep out of eyes. Rinse with water to remove.

Stop use and ask a doctor If rash occurs.

KEEP OUT OF REACH OF CHILDREN

- Keep out of rech of children. If swallowed, get medical help or contact a Poison Control Center right away.

Directions

- Apply liberally and evently 15 minutes before sun exposure.
- Reapply
- After 80 minutes of swimming or sweating
- Immediately after towel drying
- At least every 2 hours.
- Children under 6 months: ask a doctor.

Sun Protection Measure:Spending time in the sun increases your risk of skin cancer and early skin aging. To decrease this risk, regularly use a sunscreen with a broad spectrum SPF value of 15 or higher and other sun protection measures including

- Limit time in the sun, especially from 10 a.m.-2 p.m.
- Wear long-sleeved shirts, pants, hats, and sun glasses.

Other information:

Protect this product from excessive heat and direct sun.

Inactive Ingredients

Cocos Nucifera (Coconut) Oil*, Cera Alba (Beeswax)*, Simmondsia Chinensis (Jojoba) Seed Oil* (and) Calendula Officinalis Flower* (and) Chamomilla Recutita Matricaria (Chamomile) Flower*, Non-GMO Tocopherol (Vitamin E).

*CERTIFIED ORGANIC INGREDIENT

Questions or Comments?

Call (877)239-4667 M-F between 8:00am-4:00pm CST

WATER RESISTANT 80 MIN

ALL GOOD

MAKES EVERYBODY BETTER

REEF FRIENDLY

kid's mineral

sunscreen

butter stick

spf50

BROAD SPECTRUM SPF50

NET WT 2.75 OZ | 78 G

WATER/SWEAT RESISTANT (80 MIN) | CORAL REEF FRIENDLY

NON-NANO | BIODEGRADABLE

MADE IN THE USA FROM GLOBALLY SOURCED INGREDIENTS

DISTRIBUTED BY ELEMENTAL HERBS, INC.

1149 MARKET AVE., MORRO BAY, CA 93442

ALLGOODBODYCARE.COM

RECENT MAJOR CHANGES

Artowork updated to English-only vs. bilingual (English/French) used for Canadian market.